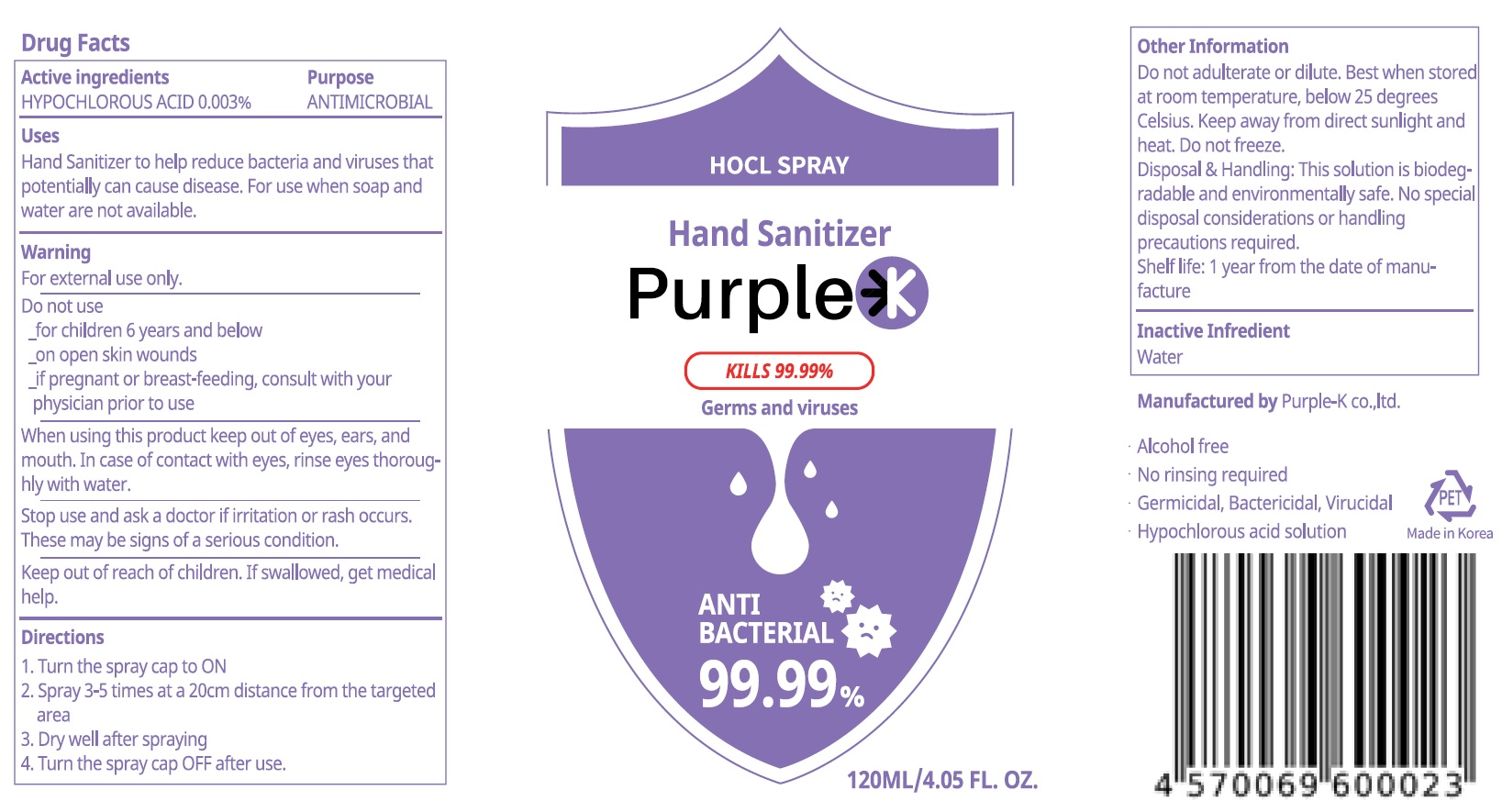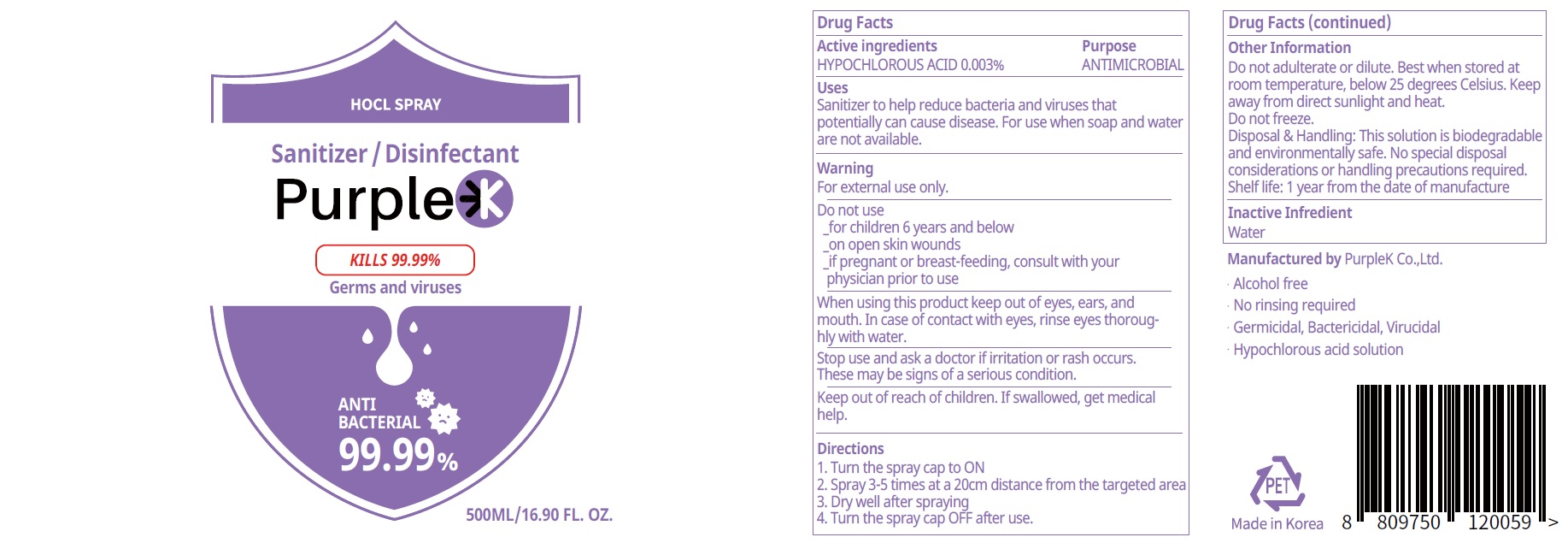 DRUG LABEL: Purple K
NDC: 81185-010 | Form: SPRAY
Manufacturer: PurpleK Co.,ltd.
Category: otc | Type: HUMAN OTC DRUG LABEL
Date: 20201201

ACTIVE INGREDIENTS: HYPOCHLOROUS ACID 0.003 g/100 mL
INACTIVE INGREDIENTS: Water

ACTIVE INGREDIENT

HYPOCHLOROUS ACID 0.003%

INACTIVE INGREDIENT

Water

PURPOSE

Antimicrobial

WARNINGS

For external use only.
Do not use
- for children 6 years and bolow
- on open skin wounds
- if pregnant or breast-feeding, comsult with your physician prior to use
When using this product keep out of eyes, ears, and mouth. In case of contact with eyes, rinse eyes thoroughly with water.
Stop use and ask a doctor if irritation or rash occurs.
These may be signs of a serious condition.
Keep out of reach of children. If swallowed, get medical help or contact a Poison Control Center right away.

Keep out of reach of children. If swallowed, get medical help or contact a Poison Control Center right away.

Uses

Hand Sanitizer to help reduce bacteria and viruses that potentially can cause disease. For use when soap and water are not available.

Directions

1. Turn the spray cap to ON
2. Spray 3-5 times at a 20cm distance from the targeted area
3. Dry well after spraying
4. Turn the spray cap OFF after use.

Other Information

Do not adulterate or dilute. Best when stored at room temperature, below 25 degrees Celsius. Keep away from direct sunlight and heat.
Do not freeze.
Disposal & Handling: This solution is biodegradable and environmentally safe. No special disposal considerations or handling precautions required.
Shelf life: 1 year from the date of manufacture